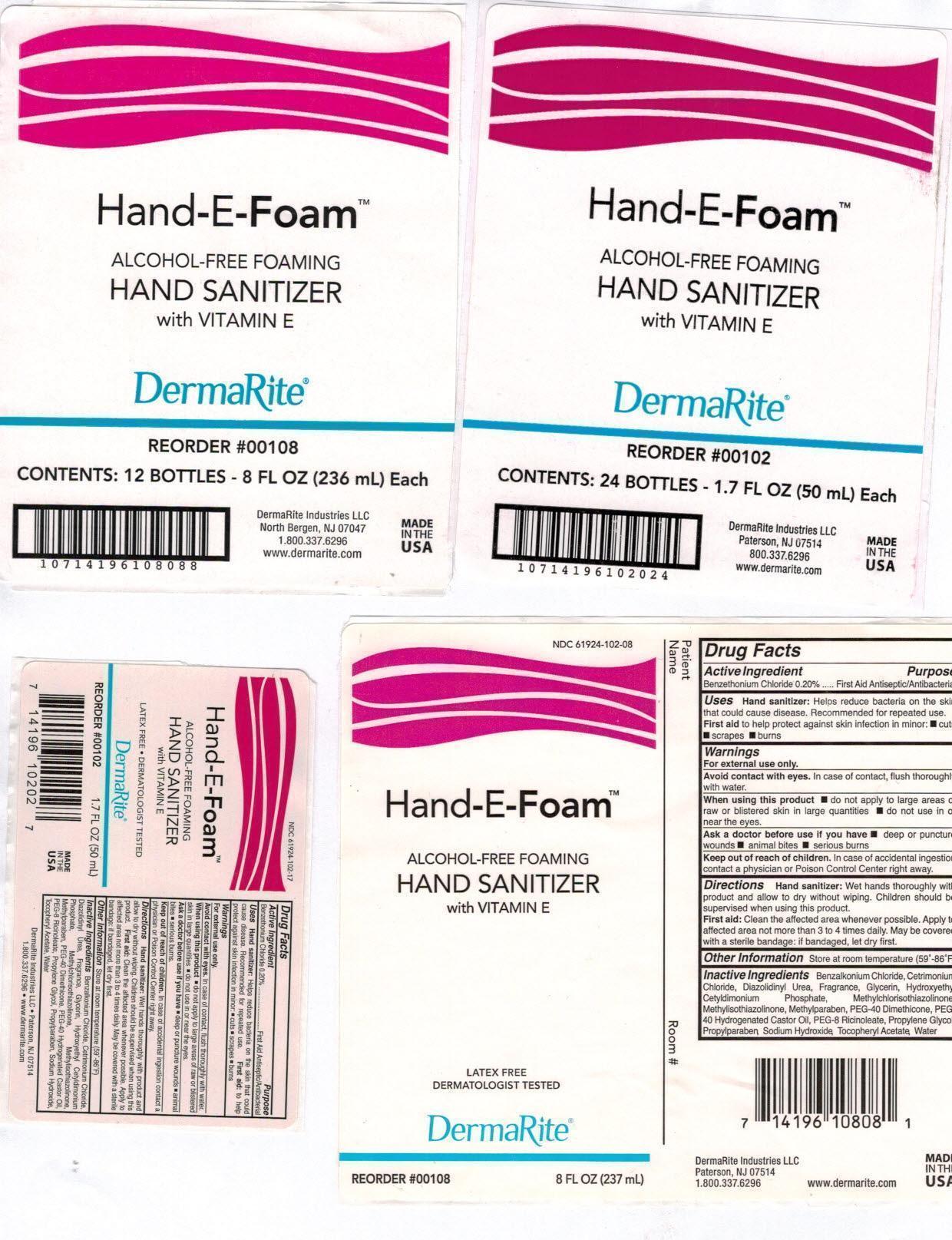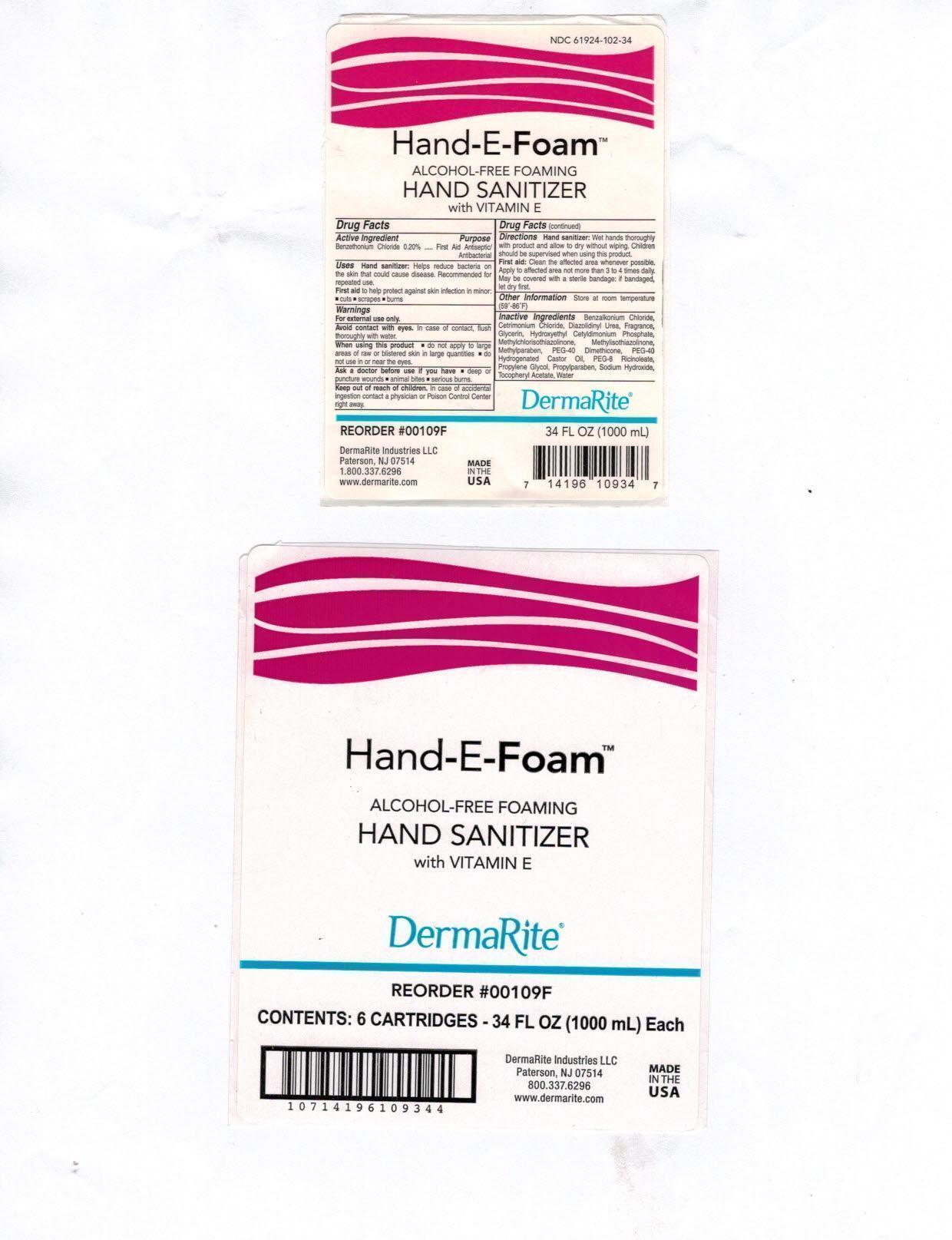 DRUG LABEL: HAND-E-FOAM
NDC: 61924-102 | Form: AEROSOL, FOAM
Manufacturer: DermaRite Industries, LLC
Category: otc | Type: HUMAN OTC DRUG LABEL
Date: 20241205

ACTIVE INGREDIENTS: BENZETHONIUM CHLORIDE 0.002 g/1 mL
INACTIVE INGREDIENTS: BENZALKONIUM CHLORIDE; CETRIMONIUM CHLORIDE; DIAZOLIDINYL UREA; GLYCERIN; HYDROXYETHYL CETYLDIMONIUM PHOSPHATE; METHYLCHLOROISOTHIAZOLINONE; METHYLISOTHIAZOLINONE; METHYLPARABEN; PEG-8 DIMETHICONE; POLYOXYL 40 HYDROGENATED CASTOR OIL; PEG-8 RICINOLEATE; PROPYLENE GLYCOL; PROPYLPARABEN; SODIUM HYDROXIDE; .ALPHA.-TOCOPHEROL ACETATE; WATER

DRUG LISTING: HAND-E-FOAM

Active Ingredient:

Benzethonium Chloride 0.20%

Purpose:

Antiseptic Handwash

Uses:

- Hand sanitizer: Helps reduce bacteria on skin that could cause disease. Recommended for repeated use.
- First aid to help protect against skin infection in minor cuts, scrapes, burns.

Warnings:

- For external use only.
- Avoid contact with eyes. In case of contact, flush thoroughly with water.
- When using this product do not apply to large area of raw or blistered skin in large quantities; do not use in or near the eyes.
- Ask a doctor before use if you have , deep of puncture wounds, animal bites, serious burns

Warnings

- Keep out of reach of children. In case of accidental ingestion contact a physician or Poison Control Center right away

Directions:

- Hand sanitizer: Wet hands thoroughly with product and allow to dry without wiping. Children should be supervised when using this product.
- First Aid: Clean the affected area whenever possible. Apply to affected area not more than 3 to 4 times daily. May be covered with a sterile bandage:if bandaged, let dry first.

Other Information:

Store at room temperature (59°-86°F)

Inactive Ingredients:

Benzalkonium Chloride, Cetrimonium Chloride, Diazolidinyl Urea, Fragrance, Glycerin, Hydroxethyl Cetyldimonium Phosphate, Methylchloroisothiazolinone, Methylisothiazolinone, Methylparaben, PEG-40 Dimethicone, PEG-40 Hydrogenated Castor Oil, PEG-8 Ricinoleate, Propylene Glycol, Propylparaben, Sodium Hydroxide, Tocopheryl Acetate, Water